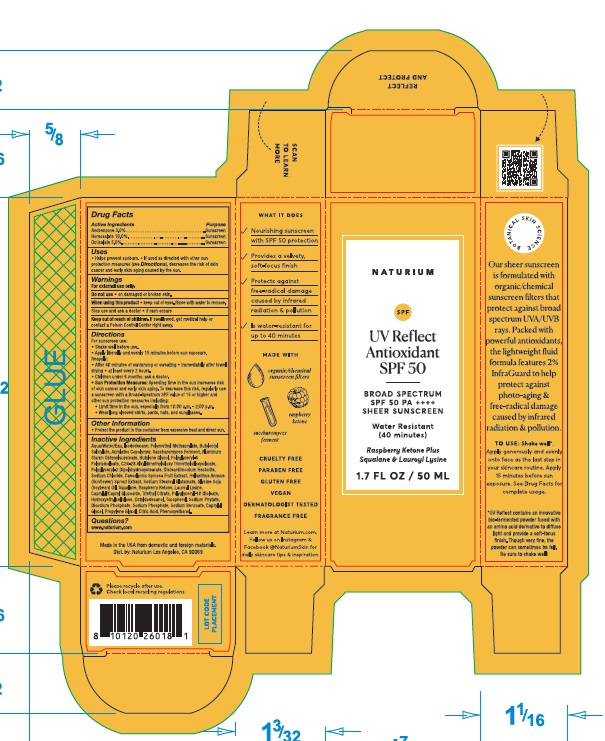 DRUG LABEL: Naturium UV Reflect Antioxidant SPF 50
NDC: 76354-125 | Form: LOTION
Manufacturer: e.l.f. Cosmetics, Inc
Category: otc | Type: HUMAN OTC DRUG LABEL
Date: 20251114

ACTIVE INGREDIENTS: AVOBENZONE 30 mg/1 mL; HOMOSALATE 100 mg/1 mL; OCTISALATE 50 mg/1 mL
INACTIVE INGREDIENTS: PHYTATE SODIUM; SODIUM PHOSPHATE, DIBASIC, ANHYDROUS; SODIUM PHOSPHATE; BUTYLENE GLYCOL; POLYGLYCERYL-6 POLYRICINOLEATE; POLYGLYCERYL-2 DIPOLYHYDROXYSTEARATE; SODIUM BENZOATE; 4-(P-HYDROXYPHENYL)-2-BUTANONE; SQUALANE; HYDROXYETHYL CELLULOSE, UNSPECIFIED; CITRIC ACID MONOHYDRATE; POLY(METHYL METHACRYLATE; 450000 MW); BUTYLOCTYL SALICYLATE; SODIUM STEAROYL GLUTAMATE; ALUMINUM STARCH OCTENYLSUCCINATE; CAPRYLYL/CAPRYL OLIGOGLUCOSIDE; PROPYLENE GLYCOL; ISODODECANE; SOYBEAN OIL; CAPRYLYL GLYCOL; SODIUM CHLORIDE; POLYGLYCERYL-10 DIOLEATE; TRIETHYL CITRATE; PHENOXYETHANOL; LAUROYL LYSINE; TOCOPHEROL; WATER; DISTEARDIMONIUM HECTORITE; OCTYLDODECANOL; HELIANTHUS ANNUUS SPROUT

Naturium UV Reflect Antioxidant SPF 50

Active Ingredients

Avobenzone 3.0%

Homosalate 10.0%

Octisalate 5.0%

Purpose

Sunscreen

Uses

- Helps prevent sunburn.
- If used as directed with other sun protection measures (see Directions), decreases the risk of skin cancer and early skin aging caused by the sun.

Warnings

For external use only.

Do not use

- on damaged or broken skin.

When using this product

- keep out of eyes. Rinse with water to remove.

Stop use and ask a doctor

- if rash occurs

Keep out of reach of children.

If swallowed, get medical help or contact a Poison Control Center right away.

Directions

For sunscreen use:

- Shake well before use.
- Apply liberally and evenly 15 minutes before sun exposure.

Reapply:

- After 40 minutes of swimming or sweating
- immediately after towel drying
- at least every 2 hours.
- Children under 6 months: ask a doctor.
- Sun Protection Measures: Spending time in the sun increases risk of skin cancer and early aging. To decrease this risk, regularly use a sunscreen with a Broad-Spectrum SPF value of 15 or higher and other sun protection measures including:
- Limit time in the sun, especially from 10:00 a.m. - 2:00 p.m.
- Wear long sleeved shirts, pants, hats, and sunglasses.

Other Information

- Protect the product in this container from excessive heat and direct sun.

Inactive Ingredients

Aqua/Water/Eau, Isododecane, Polymethyl Methacryate, Butyloctyl Salicylate, Acrylates Copolymer, Saccharomyces Ferment, Aluminum Starch Octenylsuccinate, Butylene Glycol, Polyglyceryl-6 Polyricinoleate, C24-28 Alkyldimethylsiloxy Trimethylsiloxysilicate, Polyglyceryl-2 Dipolyhydroxystearate, Disteardimonium Hectorite, Sodium Chloride, Caesalpinia Spinosa Fruit Extract, Helianthus Annuus (Sunflower) Sprout Extract, Sodium Stearoyl Glutamate, Glycine Soja (Soybean) Oil, Squalane, Raspberry Ketone, Lauroyl Lysine, Caprylyl/Capryl Glucoside, Triethyl Citrate, Polyglyceryl-10 Dioleate, Hydroxyethylcellulose, Octyldodecanol, Tocopherol, Sodium Phytate, Disodium Phosphate, Sodium Phosphate, Sodium Benzoate, Caprylyl Glycol, Propylene Glycol, Citric Acid, Phenoxyethanol.

Questions?

www.naturium.com